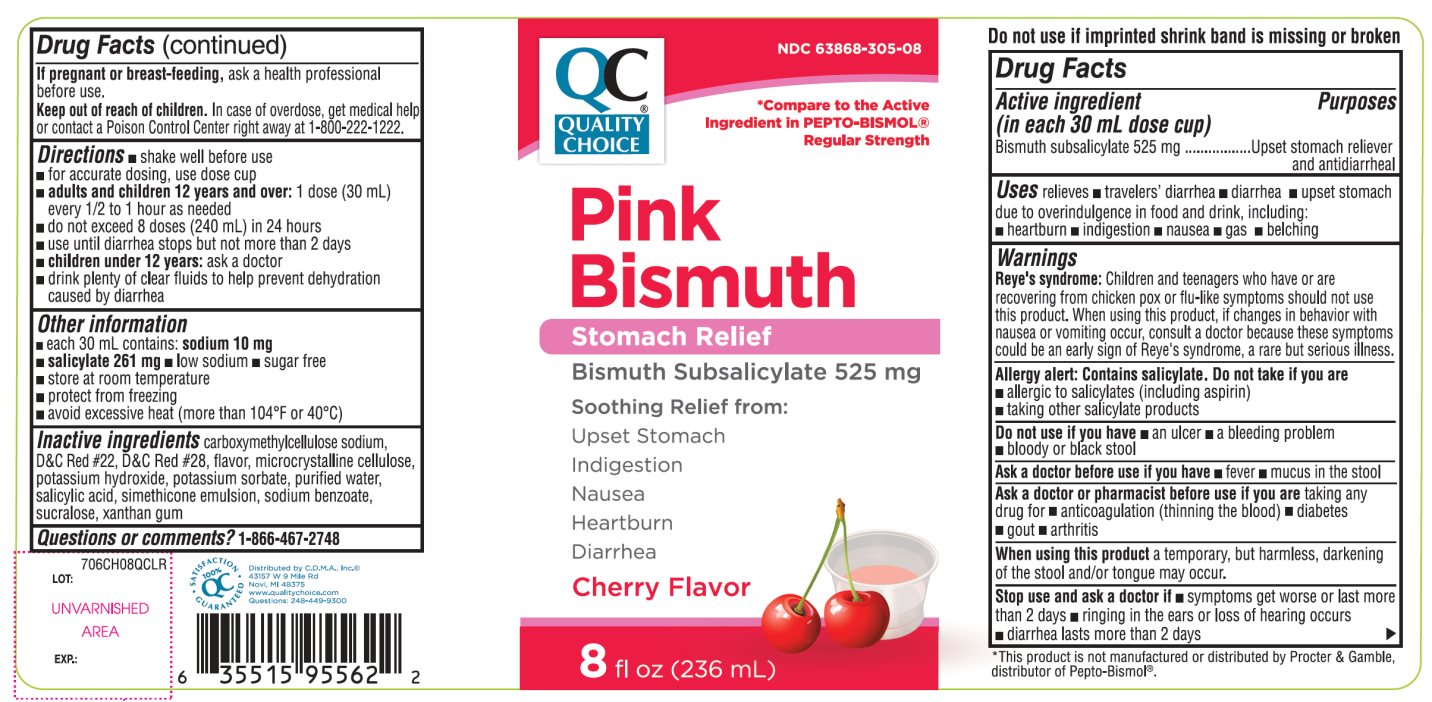 DRUG LABEL: QC Stomach Relief

NDC: 63868-305 | Form: SUSPENSION
Manufacturer: QUALITY CHOICE (CHAIN DRUG MARKETING ASSOCIATION)
Category: otc | Type: HUMAN OTC DRUG LABEL
Date: 20251204

ACTIVE INGREDIENTS: BISMUTH SUBSALICYLATE 525 mg/30 mL
INACTIVE INGREDIENTS: CARBOXYMETHYLCELLULOSE SODIUM, UNSPECIFIED; D&C RED NO. 22; D&C RED NO. 28; MICROCRYSTALLINE CELLULOSE; POTASSIUM HYDROXIDE; POTASSIUM SORBATE; WATER; SALICYLIC ACID; DIMETHICONE, UNSPECIFIED; SODIUM BENZOATE; SUCRALOSE; XANTHAN GUM

Quality Choice Stomach Relief Regular Strength Bismuth Subsalicylate 525 mg

Active ingredient (in each 30 mL dose cup)

Bismuth subsalicylate 525 mg

Purposes

Upset stomach reliever and antidiarrheal

Uses

relieves

- travelers’ diarrhea
- diarrhea
- upset stomach due to overindulgence in food and drink, including:
- heartburn
- indigestion
- nausea
- gas
- belching

Warnings

Reye’s syndrome:Children and teenagers who have or are recovering from chicken pox or flu-like symptoms should not use this product. When using this product, if changes in behavior with nausea or vomiting occur, consult a doctor because these symptoms could be an early sign of Reye’s syndrome, a rare but serious illness.

Allergy alert: Contains salicylate. Do not take if you are

- allergic to salicylates (including aspirin)
- taking other salicylate products

Do not use if you have

- an ulcer
- a bleeding problem
- bloody or black stool

Ask a doctor before use if you have

- fever
- mucus in the stool

Ask a doctor or pharmacist before use if you are

taking any drug for

- anticoagulation (thinning the blood)
- diabetes
- gout
- arthritis

When using this product

a temporary, but harmless, darkening of the stool and/or tongue may occur

Stop use and ask a doctor if

- symptoms get worse or last more than 2 days
- ringing in the ears or loss of hearing occurs
- diarrhea lasts more than 2 days

If pregnant or breast-feeding,

ask a health professional before use.

Keep out of reach of children.

In case of overdose, get medical help or contact a Poison Control Center right away (1-800-222-1222).

Directions

- shake well before use
- for accurate dosing, use dose cup
- adults and children 12 years and over:1 dose (30 mL) every 1/2 to 1 hour as needed
- do not exceed 8 doses (240 mL) in 24 hours
- use until diarrhea stops but not more than 2 days
- children under 12 years:ask a doctor
- drink plenty of clear fluids to help prevent dehydration caused by diarrhea

Other information

- each 30 mL contains:sodium 10 mg
- salicylate 261 mg
- low sodium
- sugar free
- store at room temperature
- protect from freezing
- avoid excessive heat (more than 104°F 40°C)

Inactive ingredients

carboxymethylcellulose sodium, D&C Red # 22, D&C Red # 28, flavor, microcrystalline cellulose, potassium hydroxide, potassium sorbate, purified water, salicylic acid, simethicone emulsion, sodium benzoate, sucralose, xanthan gum

Questions or comments?

1-866-467-2748

Do not use if imprinted shrink band is missing or broken.

Principal Display Panel

Quality Choice®

NDC# 63868-305-08

Compare To the Active Ingredient PEPTO-BISMOL® Regular Strength

Pink Bismuth

Stomach Relief

Bismuth Subsalicylate 525 mg

Soothing Relief from:

Upset Stomach

Indigestion

Nausea

Heartburn

Diarrhea

Regular Strength

Cherry Flavor

8 FL. OZ. (236 mL)

100% QC SATISFACTION GURANTEE

Distributed by C.D.M.A., Inc.©

43157 W 9 Mile Rd

Novi, MI 48375

www.qualitychoice.com

Questions: 248-449-9300

*This product is not manufactured or distributed by The Procter & Gamble, distributor of Pepto-Bismol®.